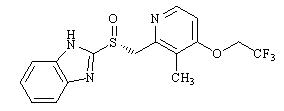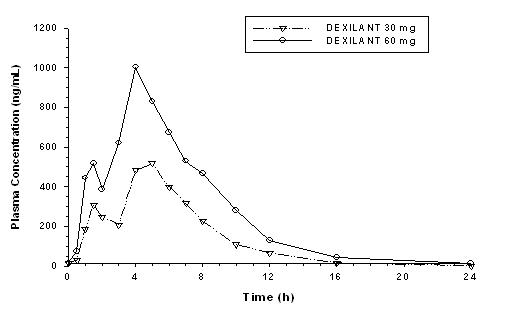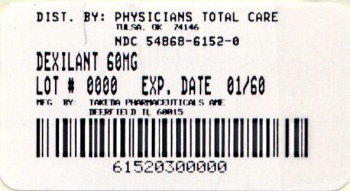 DRUG LABEL: Dexilant
NDC: 54868-6152 | Form: CAPSULE, DELAYED RELEASE
Manufacturer: Physicians Total Care, Inc.
Category: prescription | Type: HUMAN PRESCRIPTION DRUG LABEL
Date: 20120208

ACTIVE INGREDIENTS: dexlansoprazole 60 mg/1 1
INACTIVE INGREDIENTS: Methacrylic Acid - Methyl Methacrylate Copolymer (1:1); Methacrylic Acid - Methyl Methacrylate Copolymer (1:2); Methacrylic Acid - Ethyl Acrylate Copolymer (1:1) Type A; magnesium carbonate; sucrose; hydroxypropyl cellulose, low substituted; titanium dioxide; hydroxypropyl cellulose; hypromelloses; talc; polyethylene glycol 8000; triethyl citrate; polysorbate 80; silicon dioxide; carrageenan; potassium chloride; aluminum oxide; FD&C Blue No. 2

HIGHLIGHTS OF PRESCRIBING INFORMATION

These highlights do not include all the information needed to use DEXILANT safely and effectively. See full prescribing information for DEXILANT.
DEXILANT (dexlansoprazole) delayed-release capsules, for oral use
Initial U.S. Approval: 1995 (lansoprazole)

RECENT MAJOR CHANGES

Indications and Usage
Maintenance of Healed Erosive Esophagitis (1.2) | 06/2011
Warnings and Precautions
Bone Fracture (5.2) | 09/2010 05/2011

1 INDICATIONS AND USAGE

DEXILANT is a proton pump inhibitor (PPI) indicated for:

- Healing of all grades of erosive esophagitis (EE). (1.1)
- Maintaining healing of EE and relief of heartburn. (1.2)
- Treating heartburn associated with symptomatic non-erosive gastroesophageal reflux disease (GERD). (1.3)

2 DOSAGE AND ADMINISTRATION

- Healing of EE: 60 mg once daily for up to 8 weeks. (2.1)
- Maintenance of healed EE: 30 mg once daily for up to 6 months. (2.1)
- Symptomatic non-erosive GERD: 30 mg once daily for 4 weeks. (2.1)
- Hepatic impairment: Consider 30 mg maximum daily dose for patients with moderate hepatic impairment (Child-Pugh Class B). No studies were conducted in patients with severe hepatic impairment (Child-Pugh Class C). (2.2, 8.7)
- DEXILANT can be taken without regard to food. (2.3)
- DEXILANT should be swallowed whole. Alternatively, capsules can be opened, sprinkled on one tablespoon of applesauce, and swallowed immediately. (2.3)

3 DOSAGE FORMS AND STRENGTHS

- Delayed-Release Capsules: 30 mg and 60 mg. (3)

4 CONTRAINDICATIONS

Patients with known hypersensitivity to any component of the formulation. (4)

5 WARNINGS AND PRECAUTIONS

- Gastric malignancy: Symptomatic response with DEXILANT does not preclude the presence of gastric malignancy. (5.1)
- Bone Fracture: Long-term and multiple daily dose PPI therapy may be associated with an increased risk for osteoporosis-related fractures of the hip, wrist or spine. (5.2)
- Hypomagnesemia: Hypomagnesemia has been reported rarely with prolonged treatment with PPIs. (5.3)

6 ADVERSE REACTIONS

Most commonly reported adverse reactions (≥2%): diarrhea, abdominal pain, nausea, upper respiratory tract infection, vomiting, and flatulence. (6.1)

To report SUSPECTED ADVERSE REACTIONS, contact Takeda Pharmaceuticals America, Inc. at 1-877-TAKEDA-7 (1-877-825-3327) or FDA at 1-800-FDA-1088 or www.fda.gov/medwatch.

7 DRUG INTERACTIONS

- Atazanavir: Do not co-administer with DEXILANT because atazanavir systemic concentrations may be substantially decreased. (7.1)
- Drugs with pH-dependent absorption (e.g., ampicillin esters, digoxin, iron salts, ketoconazole): DEXILANT may interfere with absorption of drugs for which gastric pH is important for bioavailability. (7.1)
- Warfarin: Patients taking concomitant warfarin may require monitoring for increases in international normalized ratio (INR) and prothrombin time. (7.2)
- Tacrolimus: Concomitant tacrolimus use may increase tacrolimus whole blood concentrations. (7.3)

FULL PRESCRIBING INFORMATION

1 INDICATIONS AND USAGE

1.1 Healing of Erosive Esophagitis

DEXILANT is indicated for healing of all grades of erosive esophagitis (EE) for up to 8 weeks.

1.2 Maintenance of Healed Erosive Esophagitis

DEXILANT is indicated to maintain healing of EE and relief of heartburn for up to 6 months.

1.3 Symptomatic Non-Erosive Gastroesophageal Reflux Disease

DEXILANT is indicated for the treatment of heartburn associated with symptomatic non-erosive gastroesophageal reflux disease (GERD) for 4 weeks.

2 DOSAGE AND ADMINISTRATION

2.1 Recommended Dose

DEXILANT is available as capsules in 30 mg and 60 mg strengths for adult use. Directions for use in each indication are summarized in Table 1.

Table 1: DEXILANT Dosing Recommendations
Indication | Recommended Dose | Frequency
Healing of EE | 60 mg | Once daily for up to 8 weeks
Maintenance of Healed EE and relief of heartburn | 30 mg | Once daily
Symptomatic Non-Erosive GERD | 30 mg | Once daily for 4 weeks

2.2 Hepatic Impairment

No adjustment for DEXILANT is necessary for patients with mild hepatic impairment (Child-Pugh Class A). Consider a maximum daily dose of 30 mg for patients with moderate hepatic impairment (Child-Pugh Class B). No studies have been conducted in patients with severe hepatic impairment (Child-Pugh Class C) [see Use in Specific Populations (8.7) and Clinical Pharmacology (12.3)].

2.3 Important Administration Information

DEXILANT can be taken without regard to food.

DEXILANT should be swallowed whole.

- Alternatively, DEXILANT capsules can be administered as follows:
  - –Open capsule;
  - –Sprinkle intact granules on one tablespoon of applesauce;
  - – Swallow immediately. Granules should not be chewed.

3 DOSAGE FORMS AND STRENGTHS

- 30 mg delayed-release capsules are opaque, blue and gray with TAP and "30" imprinted on the capsule.
- 60 mg delayed-release capsules are opaque, blue with TAP and "60" imprinted on the capsule.

4 CONTRAINDICATIONS

DEXILANT is contraindicated in patients with known hypersensitivity to any component of the formulation [see Description (11)]. Hypersensitivity and anaphylaxis have been reported with DEXILANT use [see Adverse Reactions (6.1)].

5 WARNINGS AND PRECAUTIONS

5.1 Gastric Malignancy

Symptomatic response with DEXILANT does not preclude the presence of gastric malignancy.

5.2 Bone Fracture

Several published observational studies suggest that proton pump inhibitor (PPI) therapy may be associated with an increased risk for osteoporosis-related fractures of the hip, wrist or spine. The risk of fracture was increased in patients who received high-dose, defined as multiple daily doses, and long-term PPI therapy (a year or longer). Patients should use the lowest dose and shortest duration of PPI therapy appropriate to the condition being treated. Patients at risk for osteoporosis-related fractures should be managed according to established treatment guidelines [see Dosage and Administration (2) and Adverse Reactions (6)].

5.3 Hypomagnesemia

Hypomagnesemia, symptomatic and asymptomatic, has been reported rarely in patients treated with PPIs for at least three months, in most cases after a year of therapy. Serious adverse events include tetany, arrhythmias, and seizures. In most patients, treatment of hypomagnesemia required magnesium replacement and discontinuation of the PPI.

For patients expected to be on prolonged treatment or who take PPIs with medications such as digoxin or drugs that may cause hypomagnesemia (e.g., diuretics), health care professionals may consider monitoring magnesium levels prior to initiation of PPI treatment and periodically [see Adverse Reactions (6.2)].

6 ADVERSE REACTIONS

6.1 Clinical Trials Experience

Because clinical trials are conducted under widely varying conditions, adverse reaction rates observed in the clinical trials of a drug cannot be directly compared to rates in the clinical trials of another drug and may not reflect the rates observed in practice.

The safety of DEXILANT was evaluated in 4548 patients in controlled and uncontrolled clinical studies, including 863 patients treated for at least 6 months and 203 patients treated for one year. Patients ranged in age from 18 to 90 years (median age 48 years), with 54% female, 85% Caucasian, 8% Black, 4% Asian, and 3% other races. Six randomized controlled clinical trials were conducted for the treatment of EE, maintenance of healed EE, and symptomatic GERD, which included 896 patients on placebo, 455 patients on DEXILANT 30 mg, 2218 patients on DEXILANT 60 mg, and 1363 patients on lansoprazole 30 mg once daily.

Most Commonly Reported Adverse Reactions

The most common adverse reactions (≥2%) that occurred at a higher incidence for DEXILANT than placebo in the controlled studies are presented in Table 2.

Table 2: Incidence of Adverse Reactions in Controlled Studies
 | Placebo | DEXILANT 30 mg | DEXILANT 60 mg | DEXILANT Total | Lansoprazole 30 mg
Adverse Reaction | (N=896) % | (N=455) % | (N=2218) % | (N=2621) % | (N=1363) %
Diarrhea | 2.9 | 5.1 | 4.7 | 4.8 | 3.2
Abdominal Pain | 3.5 | 3.5 | 4.0 | 4.0 | 2.6
Nausea | 2.6 | 3.3 | 2.8 | 2.9 | 1.8
Upper Respiratory Tract Infection | 0.8 | 2.9 | 1.7 | 1.9 | 0.8
Vomiting | 0.8 | 2.2 | 1.4 | 1.6 | 1.1
Flatulence | 0.6 | 2.6 | 1.4 | 1.6 | 1.2

Adverse Reactions Resulting in Discontinuation

In controlled clinical studies, the most common adverse reaction leading to discontinuation from DEXILANT therapy was diarrhea (0.7%).

Other Adverse Reactions

Other adverse reactions that were reported in controlled studies at an incidence of less than 2% are listed below by body system:

Blood and Lymphatic System Disorders: anemia, lymphadenopathy

Cardiac Disorders: angina, arrhythmia, bradycardia, chest pain, edema, myocardial infarction, palpitation, tachycardia

Ear and Labyrinth Disorders: ear pain, tinnitus, vertigo

Endocrine Disorders: goiter

Eye Disorders: eye irritation, eye swelling

Gastrointestinal Disorders: abdominal discomfort, abdominal tenderness, abnormal feces, anal discomfort, Barrett's esophagus, bezoar, bowel sounds abnormal, breath odor, colitis microscopic, colonic polyp, constipation, dry mouth, duodenitis, dyspepsia, dysphagia, enteritis, eructation, esophagitis, gastric polyp, gastritis, gastroenteritis, gastrointestinal disorders, gastrointestinal hypermotility disorders, GERD, GI ulcers and perforation, hematemesis, hematochezia, hemorrhoids, impaired gastric emptying, irritable bowel syndrome, mucus stools, oral mucosal blistering, painful defecation, proctitis, paresthesia oral, rectal hemorrhage, retching

General Disorders and Administration Site Conditions: adverse drug reaction, asthenia, chest pain, chills, feeling abnormal, inflammation, mucosal inflammation, nodule, pain, pyrexia

Hepatobiliary Disorders: biliary colic, cholelithiasis, hepatomegaly

Immune System Disorders: hypersensitivity

Infections and Infestations: candida infections, influenza, nasopharyngitis, oral herpes, pharyngitis, sinusitis, viral infection, vulvo-vaginal infection

Injury, Poisoning and Procedural Complications: falls, fractures, joint sprains, overdose, procedural pain, sunburn

Laboratory Investigations: ALP increased, ALT increased, AST increased, bilirubin decreased/increased, blood creatinine increased, blood gastrin increased, blood glucose increased, blood potassium increased, liver function test abnormal, platelet count decreased, total protein increased, weight increase

Metabolism and Nutrition Disorders: appetite changes, hypercalcemia, hypokalemia

Musculoskeletal and Connective Tissue Disorders: arthralgia, arthritis, muscle cramps, musculoskeletal pain, myalgia

Nervous System Disorders: altered taste, convulsion, dizziness, headaches, migraine, memory impairment, paresthesia, psychomotor hyperactivity, tremor, trigeminal neuralgia

Psychiatric Disorders: abnormal dreams, anxiety, depression, insomnia, libido changes

Renal and Urinary Disorders: dysuria, micturition urgency

Reproductive System and Breast Disorders: dysmenorrhea, dyspareunia, menorrhagia, menstrual disorder

Respiratory, Thoracic and Mediastinal Disorders: aspiration, asthma, bronchitis, cough, dyspnoea, hiccups, hyperventilation, respiratory tract congestion, sore throat

Skin and Subcutaneous Tissue Disorders: acne, dermatitis, erythema, pruritis, rash, skin lesion, urticaria

Vascular Disorders: deep vein thrombosis, hot flush, hypertension

Additional adverse reactions that were reported in a long-term uncontrolled study and were considered related to DEXILANT by the treating physician included: anaphylaxis, auditory hallucination, B-cell lymphoma, bursitis, central obesity, cholecystitis acute, dehydration, diabetes mellitus, dysphonia, epistaxis, folliculitis, gout, herpes zoster, hyperlipidemia, hypothyroidism, increased neutrophils, MCHC decrease, neutropenia, rectal tenesmus, restless legs syndrome, somnolence, tonsillitis.

Other adverse reactions not observed with DEXILANT, but occurring with the racemate lansoprazole can be found in the lansoprazole prescribing information, ADVERSE REACTIONS section.

6.2 Postmarketing Experience

The following adverse reactions have been identified during post-approval of DEXILANT. As these reactions are reported voluntarily from a population of uncertain size, it is not always possible to reliably estimate their frequency or establish a causal relationship to drug exposure.

Blood and Lymphatic System Disorders: autoimmune hemolytic anemia, idiopathic thrombocytopenic purpura

Ear and Labyrinth Disorders: deafness

Eye Disorders: blurred vision

Gastrointestinal Disorders: oral edema, pancreatitis

General Disorders and Administration Site Conditions: facial edema

Hepatobiliary Disorders: drug-induced hepatitis

Immune System Disorders: anaphylactic shock (requiring emergency intervention), exfoliative dermatitis, Stevens-Johnson syndrome, toxic epidermal necrolysis (some fatal)

Metabolism and Nutrition Disorders: hypomagnesemia, hyponatremia

Musculoskeletal System Disorders: bone fracture

Nervous System Disorders: cerebrovascular accident, transient ischemic attack

Renal and Urinary Disorders: acute renal failure

Respiratory, Thoracic and Mediastinal Disorders: pharyngeal edema, throat tightness

Skin and Subcutaneous Tissue Disorders: generalized rash, leucocytoclastic vasculitis

7 DRUG INTERACTIONS

7.1 Drugs with pH-Dependent Absorption Pharmacokinetics

DEXILANT causes inhibition of gastric acid secretion. DEXILANT is likely to substantially decrease the systemic concentrations of the HIV protease inhibitor atazanavir, which is dependent upon the presence of gastric acid for absorption, and may result in a loss of therapeutic effect of atazanavir and the development of HIV resistance. Therefore, DEXILANT should not be co-administered with atazanavir.

DEXILANT may interfere with the absorption of other drugs where gastric pH is an important determinant of oral bioavailability (e.g., ampicillin esters, digoxin, iron salts, ketoconazole).

7.2 Warfarin

Co-administration of DEXILANT 90 mg and warfarin 25 mg did not affect the pharmacokinetics of warfarin or INR [see Clinical Pharmacology (12.3)]. However, there have been reports of increased INR and prothrombin time in patients receiving PPIs and warfarin concomitantly. Increases in INR and prothrombin time may lead to abnormal bleeding and even death. Patients treated with DEXILANT and warfarin concomitantly may need to be monitored for increases in INR and prothrombin time.

7.3 Tacrolimus

Concomitant administration of dexlansoprazole and tacrolimus may increase whole blood levels of tacrolimus, especially in transplant patients who are intermediate or poor metabolizers of CYP2C19.

7.4 Clopidogrel

Concomitant administration of dexlansoprazole and clopidogrel in healthy subjects had no clinically important effect on exposure to the active metabolite of clopidogrel or clopidogrel-induced platelet inhibition [see Clinical Pharmacology (12.3)]. No dose adjustment of clopidogrel is necessary when administered with an approved dose of DEXILANT.

8 USE IN SPECIFIC POPULATIONS

8.1 Pregnancy

Teratogenic Effects

Pregnancy Category B. There are no adequate and well-controlled studies with dexlansoprazole in pregnant women. There were no adverse fetal effects in animal reproduction studies of dexlansoprazole in rabbits. Because animal reproduction studies are not always predictive of human response, DEXILANT should be used during pregnancy only if clearly needed.

A reproduction study conducted in rabbits at oral dexlansoprazole doses up to approximately 9 times the maximum recommended human dexlansoprazole dose (60 mg per day) revealed no evidence of impaired fertility or harm to the fetus due to dexlansoprazole. In addition, reproduction studies performed in pregnant rats with oral lansoprazole at doses up to 40 times the recommended human lansoprazole dose and in pregnant rabbits at oral lansoprazole doses up to 16 times the recommended human lansoprazole dose revealed no evidence of impaired fertility or harm to the fetus due to lansoprazole [see Nonclinical Toxicology (13.2)].

8.3 Nursing Mothers

It is not known whether dexlansoprazole is excreted in human milk. However, lansoprazole and its metabolites are present in rat milk following the administration of lansoprazole. As many drugs are excreted in human milk, and because of the potential for tumorigenicity shown for lansoprazole in rat carcinogenicity studies [see Nonclinical Toxicology (13.1)], a decision should be made whether to discontinue nursing or to discontinue the drug, taking into account the importance of the drug to the mother.

8.4 Pediatric Use

Safety and effectiveness of DEXILANT in pediatric patients (less than 18 years of age) have not been established.

8.5 Geriatric Use

In clinical studies of DEXILANT, 11% of patients were aged 65 years and over. No overall differences in safety or effectiveness were observed between these patients and younger patients, and other reported clinical experience has not identified significant differences in responses between geriatric and younger patients, but greater sensitivity of some older individuals cannot be ruled out [see Clinical Pharmacology (12.3)].

8.6 Renal Impairment

No dosage adjustment of DEXILANT is necessary in patients with renal impairment. The pharmacokinetics of dexlansoprazole in patients with renal impairment are not expected to be altered since dexlansoprazole is extensively metabolized in the liver to inactive metabolites, and no parent drug is recovered in the urine following an oral dose of dexlansoprazole [see Clinical Pharmacology (12.3)].

8.7 Hepatic Impairment

No dosage adjustment for DEXILANT is necessary for patients with mild hepatic impairment (Child-Pugh Class A). DEXILANT 30 mg should be considered for patients with moderate hepatic impairment (Child-Pugh Class B). No studies have been conducted in patients with severe hepatic impairment (Child-Pugh Class C) [see Clinical Pharmacology (12.3)].

10 OVERDOSAGE

There have been no reports of significant overdose of DEXILANT. Multiple doses of DEXILANT 120 mg and a single dose of DEXILANT 300 mg did not result in death or other severe adverse events. However, serious adverse events of hypertension have been reported in association with twice daily doses of DEXILANT 60 mg. Non-serious adverse reactions observed with twice daily doses of DEXILANT 60 mg include hot flashes, contusion, oropharyngeal pain, and weight loss. Dexlansoprazole is not expected to be removed from the circulation by hemodialysis. If an overdose occurs, treatment should be symptomatic and supportive.

11 DESCRIPTION

The active ingredient in DEXILANT (dexlansoprazole) delayed-release capsules, a proton pump inhibitor, is (+)-2-[(R)-{[3-methyl-4-(2,2,2-trifluoroethoxy)pyridin-2-yl] methyl} sulfinyl]-1H-benzimidazole, a compound that inhibits gastric acid secretion. Dexlansoprazole is the R-enantiomer of lansoprazole (a racemic mixture of the R- and S-enantiomers). Its empirical formula is: C16H14F3N3O2S, with a molecular weight of 369.36. The structural formula is:

Dexlansoprazole is a white to nearly white crystalline powder which melts with decomposition at 140°C. Dexlansoprazole is freely soluble in dimethylformamide, methanol, dichloromethane, ethanol, and ethyl acetate; and soluble in acetonitrile; slightly soluble in ether; and very slightly soluble in water; and practically insoluble in hexane.

Dexlansoprazole is stable when exposed to light. Dexlansoprazole is more stable in neutral and alkaline conditions than acidic conditions.

DEXILANT is supplied as a dual delayed-release formulation in capsules for oral administration. The capsules contain dexlansoprazole in a mixture of two types of enteric-coated granules with different pH-dependent dissolution profiles [see Clinical Pharmacology (12.3)].

DEXILANT is available in two dosage strengths: 30 mg and 60 mg, per capsule. Each capsule contains enteric-coated granules consisting of dexlansoprazole (active ingredient) and the following inactive ingredients: sugar spheres, magnesium carbonate, sucrose, low-substituted hydroxypropyl cellulose, titanium dioxide, hydroxypropyl cellulose, hypromellose 2910, talc, methacrylic acid copolymers, polyethylene glycol 8000, triethyl citrate, polysorbate 80, and colloidal silicon dioxide. The components of the capsule shell include the following inactive ingredients: hypromellose, carrageenan and potassium chloride. Based on the capsule shell color, blue contains FD&C Blue No. 2 aluminum lake; gray contains black ferric oxide; and both contain titanium dioxide.

12 CLINICAL PHARMACOLOGY

12.1 Mechanism of Action

Dexlansoprazole is a PPI that suppresses gastric acid secretion by specific inhibition of the (H^+,K^+)-ATPase in the gastric parietal cell. By acting specifically on the proton pump, dexlansoprazole blocks the final step of acid production.

12.2 Pharmacodynamics

Antisecretory Activity

The effects of DEXILANT 60 mg (n=20) or lansoprazole 30 mg (n=23) once daily for five days on 24-hour intragastric pH were assessed in healthy subjects in a multiple-dose crossover study. The results are summarized in Table 3.

Table 3: Effect on 24-hour Intragastric pH on Day 5 After Administration of DEXILANT or Lansoprazole
DEXILANT 60 mg | Lansoprazole 30 mg
Mean Intragastric pH
4.55 | 4.13
% Time Intragastric pH > 4
(hours)
71 (17 hours) | 60 (14 hours)

Serum Gastrin Effects

The effect of DEXILANT on serum gastrin concentrations was evaluated in approximately 3460 patients in clinical trials up to 8 weeks and in 1023 patients for up to 6 to 12 months. The mean fasting gastrin concentrations increased from baseline during treatment with DEXILANT 30 mg and 60 mg doses. In patients treated for more than 6 months, mean serum gastrin levels increased during approximately the first 3 months of treatment and were stable for the remainder of treatment. Mean serum gastrin levels returned to pre-treatment levels within one month of discontinuation of treatment.

Enterochromaffin-Like Cell (ECL) Effects

There were no reports of ECL cell hyperplasia in gastric biopsy specimens obtained from 653 patients treated with DEXILANT 30 mg, 60 mg or 90 mg for up to 12 months.

During lifetime exposure of rats dosed daily with up to 150 mg per kg per day of lansoprazole, marked hypergastrinemia was observed followed by ECL cell proliferation and formation of carcinoid tumors, especially in female rats [see Nonclinical Toxicology (13.1)].

Effect on Cardiac Repolarization

A study was conducted to assess the potential of DEXILANT to prolong the QT/QTc interval in healthy adult subjects. DEXILANT doses of 90 mg or 300 mg did not delay cardiac repolarization compared to placebo. The positive control (moxifloxacin) produced statistically significantly greater mean maximum and time-averaged QT/QTc intervals compared to placebo.

12.3 Pharmacokinetics

The dual delayed release formulation of DEXILANT results in a dexlansoprazole plasma concentration-time profile with two distinct peaks; the first peak occurs 1 to 2 hours after administration, followed by a second peak within 4 to 5 hours (see Figure 1). Dexlansoprazole is eliminated with a half-life of approximately 1 to 2 hours in healthy subjects and in patients with symptomatic GERD. No accumulation of dexlansoprazole occurs after multiple, once daily doses of DEXILANT 30 mg or 60 mg, although mean AUCt and Cmax values of dexlansoprazole were slightly higher (less than 10%) on day 5 than on day 1.

BOXED WARNING

Figure 1: Mean Plasma Dexlansoprazole Concentration –
Time Profile Following Oral Administration of 30 or 60 mg DEXILANT
Once Daily for 5 Days in Healthy Subjects

The pharmacokinetics of dexlansoprazole are highly variable, with percent coefficient of variation (CV%) values for Cmax, AUC, and CL/F of greater than 30% (see Table 4).

Table 4: Mean (CV%) Pharmacokinetic Parameters for Subjects on Day 5 After Administration of DEXILANT
Dose (mg) | Cmax (ng/mL) | AUC24 (ng∙h/mL) | CL/F (L/h)
30 | 658 (40%) (N=44) | 3275 (47%) (N=43) | 11.4 (48%) (N=43)
60 | 1397 (51%) (N=79) | 6529 (60%) (N=73) | 11.6 (46%) (N=41)

Absorption

After oral administration of DEXILANT 30 mg or 60 mg to healthy subjects and symptomatic GERD patients, mean Cmax and AUC values of dexlansoprazole increased approximately dose proportionally (see Figure 1).

Distribution

Plasma protein binding of dexlansoprazole ranged from 96.1% to 98.8% in healthy subjects and was independent of concentration from 0.01 to 20 mcg per mL. The apparent volume of distribution (Vz/F) after multiple doses in symptomatic GERD patients was 40.3 L.

Metabolism

Dexlansoprazole is extensively metabolized in the liver by oxidation, reduction, and subsequent formation of sulfate, glucuronide and glutathione conjugates to inactive metabolites. Oxidative metabolites are formed by the cytochrome P450 (CYP) enzyme system including hydroxylation mainly by CYP2C19, and oxidation to the sulfone by CYP3A4.

CYP2C19 is a polymorphic liver enzyme which exhibits three phenotypes in the metabolism of CYP2C19 substrates; extensive metabolizers (*1/*1), intermediate metabolizers (*1/mutant) and poor metabolizers (mutant/mutant). Dexlansoprazole is the major circulating component in plasma regardless of CYP2C19 metabolizer status. In CYP2C19 intermediate and extensive metabolizers, the major plasma metabolites are 5-hydroxy dexlansoprazole and its glucuronide conjugate, while in CYP2C19 poor metabolizers dexlansoprazole sulfone is the major plasma metabolite.

Elimination

Following the administration of DEXILANT, no unchanged dexlansoprazole is excreted in urine. Following the administration of [^14C]dexlansoprazole to 6 healthy male subjects, approximately 50.7% (standard deviation (SD): 9.0%) of the administered radioactivity was excreted in urine and 47.6% (SD: 7.3%) in the feces. Apparent clearance (CL/F) in healthy subjects was 11.4 to 11.6 L/h, respectively, after 5-days of 30 or 60 mg once daily administration.

Effect of CYP2C19 Polymorphism on Systemic Exposure of Dexlansoprazole

Systemic exposure of dexlansoprazole is generally higher in intermediate and poor metabolizers. In male Japanese subjects who received a single dose of DEXILANT 30 mg or 60 mg (N=2 to 6 subjects/group), mean dexlansoprazole Cmax and AUC values were up to 2 times higher in intermediate compared to extensive metabolizers; in poor metabolizers, mean Cmax was up to 4 times higher and mean AUC was up to 12 times higher compared to extensive metabolizers. Though such study was not conducted in Caucasians and African Americans, it is expected dexlansoprazole exposure in these races will be affected by CYP2C19 phenotypes as well.

Effect of Food on Pharmacokinetics and Pharmacodynamics

In food-effect studies in healthy subjects receiving DEXILANT under various fed conditions compared to fasting, increases in Cmax ranged from 12% to 55%, increases in AUC ranged from 9% to 37%, and tmax varied (ranging from a decrease of 0.7 hours to an increase of 3 hours). No significant differences in mean intragastric pH were observed between fasted and various fed conditions. However, the percentage of time intragastric pH exceeded 4 over the 24-hour dosing interval decreased slightly when DEXILANT was administered after a meal (57%) relative to fasting (64%), primarily due to a decreased response in intragastric pH during the first 4 hours after dosing. Because of this, while DEXILANT can be taken without regard to food, some patients may benefit from administering the dose prior to a meal if post-meal symptoms do not resolve under post-fed conditions.

Special Populations

Pediatric Use

The pharmacokinetics of dexlansoprazole in patients under the age of 18 years have not been studied.

Geriatric Use

The terminal elimination half-life of dexlansoprazole is significantly increased in geriatric subjects compared to younger subjects (2.23 and 1.5 hours, respectively); this difference is not clinically relevant. Dexlansoprazole exhibited higher systemic exposure (AUC) in geriatric subjects (34.5% higher) than younger subjects. No dosage adjustment is needed in geriatric patients [see Use in Specific Populations (8.5)].

Renal Impairment

Dexlansoprazole is extensively metabolized in the liver to inactive metabolites, and no parent drug is recovered in the urine following an oral dose of dexlansoprazole. Therefore, the pharmacokinetics of dexlansoprazole are not expected to be altered in patients with renal impairment, and no studies were conducted in subjects with renal impairment [see Use in Specific Populations (8.6)]. In addition, the pharmacokinetics of lansoprazole were studied in patients with mild, moderate or severe renal impairment; results demonstrated no need for a dose adjustment for this patient population.

Hepatic Impairment

In a study of 12 patients with moderately impaired hepatic function who received a single oral dose of DEXILANT 60 mg, plasma exposure (AUC) of bound and unbound dexlansoprazole in the hepatic impairment group was approximately 2 times greater compared to subjects with normal hepatic function. This difference in exposure was not due to a difference in protein binding between the two liver function groups. No adjustment for DEXILANT is necessary for patients with mild hepatic impairment (Child-Pugh Class A). DEXILANT 30 mg should be considered for patients with moderate hepatic impairment (Child-Pugh Class B). No studies have been conducted in patients with severe hepatic impairment (Child-Pugh Class C) [see Use in Specific Populations (8.7)].

Gender

In a study of 12 male and 12 female healthy subjects who received a single oral dose of DEXILANT 60 mg, females had higher systemic exposure (AUC) (42.8% higher) than males. No dosage adjustment is necessary in patients based on gender.

Drug-Drug Interactions

Warfarin

In a study of 20 healthy subjects, co-administration of DEXILANT 90 mg once daily for 11 days with a single 25 mg oral dose of warfarin on day 6 did not result in any significant differences in the pharmacokinetics of warfarin or INR compared to administration of warfarin with placebo. However, there have been reports of increased INR and prothrombin time in patients receiving PPIs and warfarin concomitantly [see Drug Interactions (7.2)].

Cytochrome P 450 Interactions

Dexlansoprazole is metabolized, in part, by CYP2C19 and CYP3A4 [see Clinical Pharmacology (12.3)].

In vitro studies have shown that dexlansoprazole is not likely to inhibit CYP isoforms 1A1, 1A2, 2A6, 2B6, 2C8, 2C9, 2D6, 2E1 or 3A4. As such, no clinically relevant interactions with drugs metabolized by these CYP enzymes would be expected. Furthermore, in vivo studies showed that DEXILANT did not have an impact on the pharmacokinetics of coadministered phenytoin (CYP2C9 substrate) or theophylline (CYP1A2 substrate). The subjects' CYP1A2 genotypes in the drug-drug interaction study with theophylline were not determined. Although in vitro studies indicated that DEXILANT has the potential to inhibit CYP2C19 in vivo, an in vivo drug-drug interaction study in mainly CYP2C19 extensive and intermediate metabolizers has shown that DEXILANT does not affect the pharmacokinetics of diazepam (CYP2C19 substrate).

Clopidogrel

Clopidogrel is metabolized to its active metabolite in part by CYP2C19. A study of healthy subjects who were CYP2C19 extensive metabolizers, receiving once daily administration of clopidogrel 75 mg alone or concomitantly with DEXILANT 60 mg (n=40), for 9 days was conducted. The mean AUC of the active metabolite of clopidogrel was reduced by approximately 9% (mean AUC ratio was 91%, with 90% CI of 86-97%) when DEXILANT was coadministered compared to administration of clopidogrel alone. Pharmacodynamic parameters were also measured and demonstrated that the change in inhibition of platelet aggregation (induced by 5 mcM ADP) was related to the change in the exposure to clopidogrel active metabolite. The clinical significance of this finding is not clear.

13 NONCLINICAL TOXICOLOGY

13.1 Carcinogenesis, Mutagenesis, Impairment of Fertility

The carcinogenic potential of dexlansoprazole was assessed using lansoprazole studies. In two 24-month carcinogenicity studies, Sprague-Dawley rats were treated orally with lansoprazole at doses of 5 to 150 mg per kg per day, about 1 to 40 times the exposure on a body surface (mg/m^2) basis of a 50 kg person of average height [1.46 m^2 body surface area (BSA)] given the recommended human dose of lansoprazole 30 mg per day.

Lansoprazole produced dose-related gastric ECL cell hyperplasia and ECL cell carcinoids in both male and female rats [see Clinical Pharmacology (12.2)].

In rats, lansoprazole also increased the incidence of intestinal metaplasia of the gastric epithelium in both sexes. In male rats, lansoprazole produced a dose-related increase of testicular interstitial cell adenomas. The incidence of these adenomas in rats receiving doses of 15 to 150 mg per kg per day (4 to 40 times the recommended human lansoprazole dose based on BSA) exceeded the low background incidence (range = 1.4 to 10%) for this strain of rat.

In a 24-month carcinogenicity study, CD-1 mice were treated orally with lansoprazole doses of 15 to 600 mg per kg per day, 2 to 80 times the recommended human lansoprazole dose based on BSA. Lansoprazole produced a dose-related increased incidence of gastric ECL cell hyperplasia. It also produced an increased incidence of liver tumors (hepatocellular adenoma plus carcinoma). The tumor incidences in male mice treated with 300 and 600 mg lansoprazole per kg per day (40 to 80 times the recommended human lansoprazole dose based on BSA) and female mice treated with 150 to 600 mg lansoprazole per kg per day (20 to 80 times the recommended human lansoprazole dose based on BSA) exceeded the ranges of background incidences in historical controls for this strain of mice. Lansoprazole treatment produced adenoma of rete testis in male mice receiving 75 to 600 mg per kg per day (10 to 80 times the recommended human lansoprazole dose based on BSA).

A 26-week p53 (+/-) transgenic mouse carcinogenicity study of lansoprazole was not positive.

Lansoprazole was positive in the Ames test and the in vitro human lymphocyte chromosomal aberration assay. Lansoprazole was not genotoxic in the ex vivo rat hepatocyte unscheduled DNA synthesis (UDS) test, the in vivo mouse micronucleus test or the rat bone marrow cell chromosomal aberration test.

Dexlansoprazole was positive in the Ames test and in the in vitro chromosome aberration test using Chinese hamster lung cells. Dexlansoprazole was negative in the in vivo mouse micronucleus test.

The potential effects of dexlansoprazole on fertility and reproductive performance were assessed using lansoprazole studies. Lansoprazole at oral doses up to 150 mg per kg per day (40 times the recommended human lansoprazole dose based on BSA) was found to have no effect on fertility and reproductive performance of male and female rats.

13.2 Animal Toxicology and/or Pharmacology

Reproductive Toxicology Studies

A reproduction study conducted in rabbits at oral dexlansoprazole doses up to 30 mg per kg per day (approximately 9 times the maximum recommended human dexlansoprazole dose [60 mg per day] based on BSA) revealed no evidence of impaired fertility or harm to the fetus due to dexlansoprazole. In addition, reproduction studies performed in pregnant rats with oral lansoprazole at doses up to 150 mg per kg per day (40 times the recommended human lansoprazole dose based on BSA) and in pregnant rabbits at oral lansoprazole doses up to 30 mg per kg per day (16 times the recommended human lansoprazole dose based on BSA) revealed no evidence of impaired fertility or harm to the fetus due to lansoprazole.

14 CLINICAL STUDIES

14.1 Healing of Erosive Esophagitis

Two multi-center, double-blind, active-controlled, randomized, 8-week studies were conducted in patients with endoscopically confirmed EE. Severity of the disease was classified based on the Los Angeles Classification Grading System (Grades A-D). Patients were randomized to one of the following three treatment groups: DEXILANT 60 mg daily, DEXILANT 90 mg daily or lansoprazole 30 mg daily. Patients who were H. pylori positive or who had Barrett's Esophagus and/or definite dysplastic changes at baseline were excluded from these studies. A total of 4092 patients were enrolled and ranged in age from 18 to 90 years (median age 48 years) with 54% male. Race was distributed as follows: 87% Caucasian, 5% Black and 8% other. Based on the Los Angeles Classification, 71% of patients had mild EE (Grades A and B) and 29% of patients had moderate to severe EE (Grades C and D) before treatment.

The studies were designed to test non-inferiority. If non-inferiority was demonstrated then superiority would be tested. Although non-inferiority was demonstrated in both studies, the finding of superiority in one study was not replicated in the other.

The proportion of patients with healed EE at week 4 or 8 is presented below in Table 5.

Table 5: EE Healing Rates: All Grades
Study | Number of Patients (N) | Treatment Group (daily) | Week 4 % Healed | Week 8 % Healed | (95% CI) for the Treatment Difference (DEXILANT– Lansoprazole) by Week 8
1 | 657 | DEXILANT 60 mg | 70 | 87 | (-1.5, 6.1) [Demonstrated non-inferiority to lansoprazole]
1 | 648 | Lansoprazole 30 mg | 65 | 85 | (-1.5, 6.1) [Demonstrated non-inferiority to lansoprazole]
2 | 639 | DEXILANT 60 mg | 66 | 85 | (2.2, 10.5)
2 | 656 | Lansoprazole 30 mg | 65 | 79 | (2.2, 10.5)
CI = Confidence interval

DEXILANT 90 mg was studied and did not provide additional clinical benefit over DEXILANT 60 mg.

14.2 Maintenance of Healed Erosive Esophagitis

A multi-center, double-blind, placebo-controlled, randomized study was conducted in patients who successfully completed an EE study and showed endoscopically confirmed healed EE. Maintenance of healing and symptom resolution over a six-month period were evaluated with DEXILANT 30 mg or 60 mg once daily compared to placebo. A total of 445 patients were enrolled and ranged in age from 18 to 85 years (median age 49 years), with 52% female. Race was distributed as follows: 90% Caucasian, 5% Black and 5% other.

Sixty-six percent of patients treated with 30 mg of DEXILANT remained healed over the six-month time period as confirmed by endoscopy (see Table 6).

Table 6: Maintenance Rates of Healed EE at Month 6
Number of Patients (N) | Treatment Group (daily) | Maintenance Rate (%)
125 | DEXILANT 30 mg | 66.4
119 | Placebo | 14.3

DEXILANT 60 mg was studied and did not provide additional clinical benefit over DEXILANT 30 mg.

The effect of DEXILANT 30 mg on maintenance of relief of heartburn was also evaluated. Upon entry into the maintenance study, a majority of patients' baseline heartburn severity was rated as none. DEXILANT 30 mg demonstrated a statistically significantly higher percent of 24-hour heartburn-free periods compared to placebo over the 6-month treatment period (see Table 7). The majority of patients treated with placebo discontinued due to relapse of EE between month two and month six.

Table 7: Median Percentage of 24-Hour Heartburn-Free Periods of the Maintenance of Healed EE Study
 | Overall Treatment |  | Month 1 |  | Month 6
Treatment Group (daily) | N | Heartburn-Free 24-hour Periods (%) | N | Heartburn-Free 24-hour Periods (%) | N | Heartburn-Free 24-hour Periods (%)
DEXILANT 30 mg | 132 | 96.1 | 126 | 96.7 | 80 | 98.3
Placebo | 141 | 28.6 | 117 | 28.6 | 23 | 73.3

14.3 Symptomatic Non-Erosive GERD

A multi-center, double-blind, placebo-controlled, randomized, 4-week study was conducted in patients with a diagnosis of symptomatic non-erosive GERD made primarily by presentation of symptoms. These patients who identified heartburn as their primary symptom, had a history of heartburn for 6 months or longer, had heartburn on at least 4 of 7 days immediately prior to randomization and had no esophageal erosions as confirmed by endoscopy. However, patients with symptoms which were not acid-related may not have been excluded using these inclusion criteria. Patients were randomized to one of the following treatment groups: DEXILANT 30 mg daily, 60 mg daily, or placebo. A total of 947 patients were enrolled and ranged in age from 18 to 86 years (median age 48 years) with 71% female. Race was distributed as follows: 82% Caucasian, 14% Black and 4% other.

DEXILANT 30 mg provided statistically significantly greater percent of days with heartburn-free 24-hour periods over placebo as assessed by daily diary over 4 weeks (see Table 8). DEXILANT 60 mg was studied and provided no additional clinical benefit over DEXILANT 30 mg.

Table 8: Median Percentages of 24-Hour Heartburn-Free Periods During the 4 Week Treatment Period of the Symptomatic Non-Erosive GERD Study
N | Treatment Group (daily) | Heartburn-Free 24-hour Periods (%)
312 | DEXILANT 30 mg | 54.9
310 | Placebo | 18.5

A higher percentage of patients on DEXILANT 30 mg had heartburn-free 24-hour periods compared to placebo as early as the first three days of treatment and this was sustained throughout the treatment period (percentage of patients on Day 3: DEXILANT 38% versus placebo 15%; on Day 28: DEXILANT 63% versus placebo 40%).

16 HOW SUPPLIED/STORAGE AND HANDLING

DEXILANT delayed-release capsules, 60 mg, are opaque, blue with TAP and "60" imprinted on the capsule and supplied as:

NDC Number | Size
54868-6152-0 | Bottle of 30

STORAGE AND HANDLING

Store at 25°C (77°F); excursions permitted to 15-30°C (59-86°F) [see USP Controlled Room Temperature].

17 PATIENT COUNSELING INFORMATION

"See FDA-Approved Patient Labeling (Patient Information)"

To ensure the safe and effective use of DEXILANT, this information and instructions provided in the FDA-approved Patient Information Leaflet should be discussed with the patient.

Inform the patient to watch for signs of an allergic reaction as these could be serious and may require that DEXILANT be discontinued.

Advise the patient to immediately report and seek care for any cardiovascular or neurological symptoms including palpitations, dizziness, seizures, and tetany as these may be signs of hypomagnesemia [see Warnings and Precautions (5.3)].

Advise the patient to tell their health care provider if they take atazanavir, tacrolimus, warfarin and drugs that are affected by gastric pH changes [see Drug Interactions (7)]

Advise the patient to follow the dosing instructions in the Patient Information Leaflet and inform the patient that:

- DEXILANT is available as a delayed-release capsule.
- DEXILANT may be taken without regard to food.
- DEXILANT should be swallowed whole.
- Alternatively, DEXILANT capsules can be administered as follows:
  - –Open capsule;
  - –Sprinkle intact granules on one tablespoon of applesauce;
  - –Swallow immediately. Granules should not be chewed.
  - –Do not store for later use.

FDA-Approved Patient Labeling

Patient Information

DEXILANT (decks-ĭ-launt)
(dexlansoprazole)
delayed-release capsules

Read the Patient Information that comes with DEXILANT before you start taking it and each time you get a refill. There may be new information. This information does not take the place of talking with your doctor about your medical condition or your treatment.

What is DEXILANT?

DEXILANT is a prescription medicine called a proton pump inhibitor (PPI). DEXILANT reduces the amount of acid in your stomach.

DEXILANT is used in adults:

- for up to 8 weeks to heal acid-related damage to the lining of the esophagus (called erosive esophagitis or EE).
- for up to 6 months to continue healing of erosive esophagitis and relief of heartburn.
- for 4 weeks to treat heartburn related to gastroesophageal reflux disease (GERD).

GERD happens when acid from your stomach enters the tube (esophagus) that connects your mouth to your stomach. This may cause a burning feeling in your chest or throat, sour taste or burping.

In some cases, acid can damage the lining of your esophagus. This damage is called erosive esophagitis or EE.

DEXILANT may help your acid-related symptoms, but you could still have serious stomach problems. Talk with your doctor.

It is not known if DEXILANT is safe and effective in children under 18 years of age.

Who should not take DEXILANT?

Do not take DEXILANT if you are allergic to DEXILANT or any of its ingredients. See the end of this leaflet for a complete list of ingredients in DEXILANT.

What should I tell my doctor before taking DEXILANT?

Before you take DEXILANT, tell your doctor if you:

- have been told that you have low magnesium levels in your blood
- have liver problems
- have any other medical conditions
- are pregnant or plan to become pregnant. It is not known if DEXILANT will harm your unborn baby. Talk to your doctor if you are pregnant or plan to become pregnant.
- are breast-feeding or planning to breast-feed. You and your doctor should decide if you will take DEXILANT or breast-feed. You should not do both without first talking with your doctor.

Tell your doctor about all the medicines you take, including prescription and non-prescription medicines, vitamins, and herbal supplements. DEXILANT may affect how other medicines work, and other medicines may affect how DEXILANT works. Especially tell your doctor if you take:

- ampicillin sodium (Unasyn) or ampicillin trihydrate (Principen)
- atazanavir (Reyataz)
- digoxin (Lanoxin)
- a product that contains iron
- ketoconazole (Nizoral)
- warfarin (Coumadin, Jantoven)
- tacrolimus (Prograf)

Ask your doctor or pharmacist if you are not sure if your medicine is listed above.

How should I take DEXILANT?

- Take DEXILANT exactly as prescribed by your doctor.
- Do not change your dose or stop taking DEXILANT without talking to your doctor first.
- You can take DEXILANT with or without food.
- Swallow DEXILANT capsules whole.
- If you have trouble swallowing DEXILANT capsules whole, you can open the capsules and sprinkle the contents on a tablespoon of applesauce. Be sure to swallow the applesauce mixture right away. Do not chew the mixture. Do not store for later use.
- If you miss a dose, take it as soon as you remember. If it is almost time for your next dose, skip the missed dose. Just take the next dose at your regular time. Do not take 2 doses at the same time. If you are not sure about dosing, call your doctor.
- If you take too much DEXILANT, call your doctor right away or go to the nearest hospital or emergency room.

What are the possible side effects of DEXILANT?

The most common side effects of DEXILANT include:

- diarrhea
- stomach pain
- nausea
- common cold
- vomiting
- gas

Other side effects

Serious allergic reactions. Tell your doctor if you get any of the following symptoms with DEXILANT:

- rash
- face swelling
- throat tightness
- difficulty breathing

Your doctor may stop DEXILANT if these symptoms happen.

- Low magnesium levels in your body. This problem can be serious. Low magnesium can happen in some people who take a proton pump inhibitor medicine for at least 3 months. If low magnesium levels happen, it is usually after a year of treatment. You may or may not have symptoms of low magnesium.

Tell your doctor right away if you have any of these symptoms:

- seizures
- dizziness
- abnormal or fast heartbeat
- jitteriness
- jerking movements or shaking (tremors)
- muscle weakness
- spasms of the hands and feet
- cramps or muscle aches
- spasm of the voice box

Your doctor may check the level of magnesium in your body before you start taking DEXILANT, or during treatment, if you will be taking DEXILANT for a long period of time.

Bone fractures. People who are taking multiple daily doses of proton pump inhibitor medicines for a long period of time may have an increased risk of fractures of the hip, wrist or spine.

Tell your doctor if you have any side effect that bothers you or that does not go away. These are not all the possible side effects of DEXILANT. For more information, ask your doctor or pharmacist. Call your doctor for medical advice about side effects. You may report side effects to FDA at 1-800-FDA-1088.

How should I store DEXILANT?

- Store DEXILANT at room temperature between 59°F to 86°F (15°C to 30°C).

Keep DEXILANT and all medicines out of the reach of children.

General information about DEXILANT

Medicines are sometimes prescribed for purposes other than those listed in a Patient Information Leaflet. Do not use DEXILANT for a condition for which it was not prescribed. Do not give DEXILANT to other people, even if they have the same symptoms you have. It may harm them.

This Patient Information Leaflet provides a summary of the most important information about DEXILANT. If you would like more information, talk with your doctor. You can ask your doctor or pharmacist for information that is written for healthcare professionals.

For more information, go to www.DEXILANT.com or call 1-877-825-3327.

What are the ingredients in DEXILANT?

Active ingredient: dexlansoprazole.

Inactive ingredients: sugar spheres, magnesium carbonate, sucrose, low-substituted hydroxypropyl cellulose, titanium dioxide, hydroxypropyl cellulose, hypromellose 2910, talc, methacrylic acid copolymers, polyethylene glycol 8000, triethyl citrate, polysorbate 80, and colloidal silicon dioxide. The capsule shell is made of hypromellose, carrageenan and potassium chloride. Based on the capsule shell color, blue contains FD&C Blue No. 2 aluminum lake; gray contains black ferric oxide; and both contain titanium dioxide.

This Patient Information has been approved by the U.S. Food and Drug Administration.

Distributed by
Takeda Pharmaceuticals America, Inc.
Deerfield, IL 60015

DEXILANT is a trademark of Takeda Pharmaceuticals North America, Inc. and used under license by Takeda Pharmaceuticals America, Inc. Trademark registered with the U.S. Patent and Trademark office.

All other trademark names are the property of their respective owners.

©2009-2011 Takeda Pharmaceuticals America, Inc.

DEX006 R15
Revised: October 2011

Additional barcode labeling by:
Physicians Total Care, Inc.
Tulsa, Oklahoma 74146

PRINCIPAL DISPLAY PANEL - 60 mg Capsule Bottle Label

NDC 54868-6152-0

30 Capsules

DEXILANT
dexlansoprazole
delayed release
capsules

Rx only
60 mg